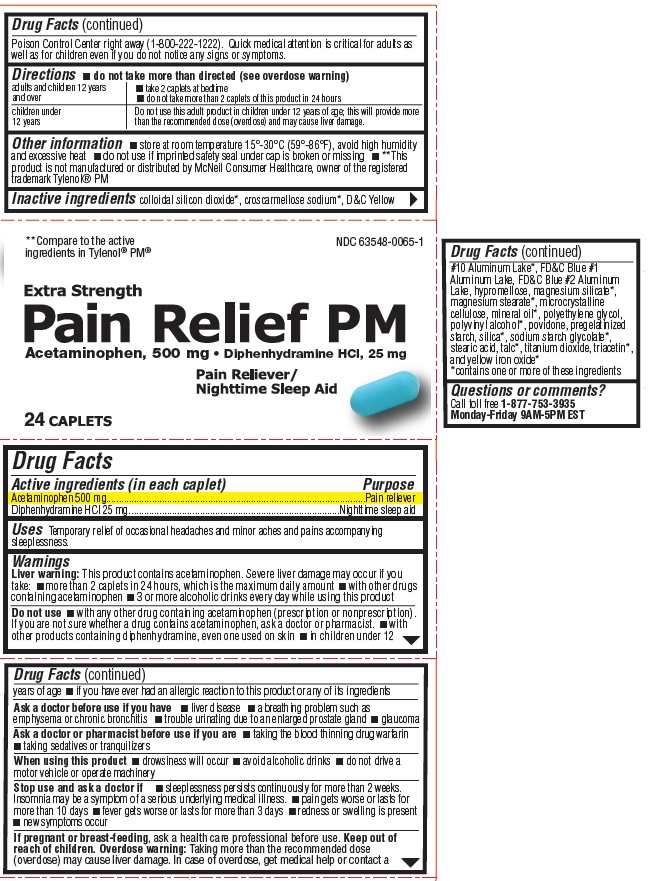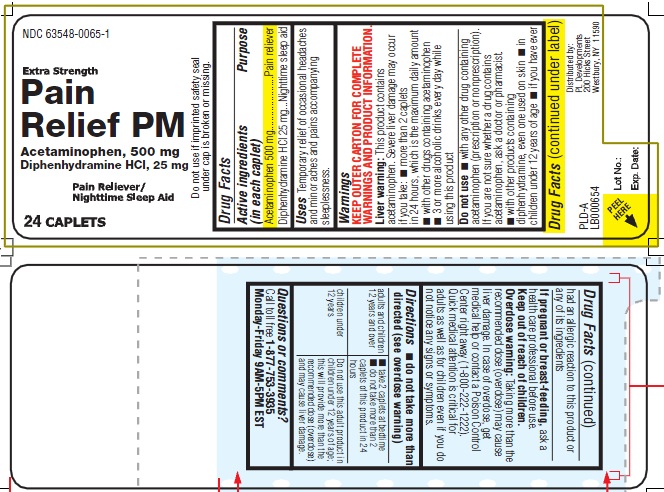 DRUG LABEL: Pain Relief PM
NDC: 63548-0065 | Form: TABLET, COATED
Manufacturer: Avema Pharma Solutions
Category: otc | Type: HUMAN OTC DRUG LABEL
Date: 20120514

ACTIVE INGREDIENTS: ACETAMINOPHEN 500 mg/1 1; DIPHENHYDRAMINE HYDROCHLORIDE 25 mg/1 1
INACTIVE INGREDIENTS: SILICON DIOXIDE; CROSCARMELLOSE SODIUM; D&C YELLOW NO. 10; FD&C BLUE NO. 1; HYPROMELLOSES; CELLULOSE, MICROCRYSTALLINE; MINERAL OIL; POLYETHYLENE GLYCOLS; POLYVINYL ALCOHOL; POVIDONE; SILICON DIOXIDE; SODIUM STARCH GLYCOLATE TYPE A CORN; STEARIC ACID; TALC; TITANIUM DIOXIDE; TRIACETIN; FERRIC OXIDE YELLOW

Extra Strength Pain Relief PM

Active ingredients (in each caplet)

Acetaminophen 500 mg

Diphenhydramine HCl 25 mg

Purpose

Pain reliever

Nighttime sleep aid

Uses

Temporary relief of occasional headaches, minor aches, and pains accompanying sleeplessness.

Warnings

Liver warning: This product contains acetaminophen. Severe liver damage may occur with this product if you take:

- more than 2 caplets in 24 hours, which is the maximum daily amount
- with other drugs containing acetaminophen
- 3 or more alcoholic drinks every day while using this product

Do not use

- with other products containing acetaminophen (prescription or nonprescription). If you are not sure whether a drug contains acetaminophen, ask a doctor or pharmacist.
- in children under 12 years of age
- if you have ever had an allergic reaction to this product or any of its ingredients

Ask a doctor before use if you have

- liver disease
- asthma
- breathing problems such as emphysema or chronic bronchitis
- glaucoma
- difficulty in urinating due to an enlargement of the prostate gland

Ask a doctor or pharmacist before use if you are

- taking the blood thinning drug warfarin
- taking sedatives or tranquilizers

When using this product

- drowsiness will occur
- avoid alcoholic drinks
- do not drive a motor vehicle or operate machinery

Stop use and ask a doctor if

- sleeplessness persists continuously for more than 2 weeks. Insomnia may be a symptom of a serious underlying medical illness.
- pain gets worse or lasts for more than 10 days
- fever gets worse or lasts for more than 3 days
- redness or swelling is present
- new symptoms occur

PREGNANCY OR BREAST FEEDING

If pregnant or breast-feeding, ask a health care professional before use.

KEEP OUT OF REACH OF CHILDREN

Overdose warning: Taking more than the recommended dose (overdose) may cause liver damage. In case of overdose, get medical help or contact a Poison Control Center right away (1-800-222-1222). Quick medical attention is critical for adults as well as for children even if you do not notice any signs or symptoms.

Directions

- do not take more than directed
- adults and children 12 years and over: take 2 caplets at bedtime. Do not take more than 2 caplets of this product in 24 hours.
- children under 12 years: do not use this product in children under 12 years of age. This will provide more than the recommended dose (overdose) and may cause liver damage.

Other information

- store at room temperature 15°-30°C (59°-86°F), avoid high humidity and excessive heat
- do not use if imprinted safety seal under cap is broken or missing
- **This product is not manufactured or distributed by McNeil Consumer Healthcare, owner of the registered
  trademark Tylenol® PM

Inactive ingredients

colloidal silicon dioxide*, croscarmellose sodium*, Dand C Yellow No. 10 Aluminum Lake*, FDandC Blue No.1 Aluminum Lake, FDandC Blue No. 2 Aluminum Lake, hypromellose, magnesium silicate*, magnesium stearate*, microcrystalline cellulose, mineral oil*, polyethylene glycol,
polyvinyl alcohol*, povidone, pregelatinized starch, silica*, sodium starch glycolate*, stearic acid, talc*, titanium dioxide, triacetin*, and yellow iron oxide*
*contains one or more of these ingredients

Product Labeling

**Compare to the active
ingredients in Tylenol® PM®

EXTRA STRENGTH

Pain Relief PM

Acetaminophen 500 mg, Diphenhydramine HCl 25 mg

Pain reliever /
Nighttime Sleep-Aid

24 CAPLETS

Do not use if imprinted safety seal under cap is broken or missing